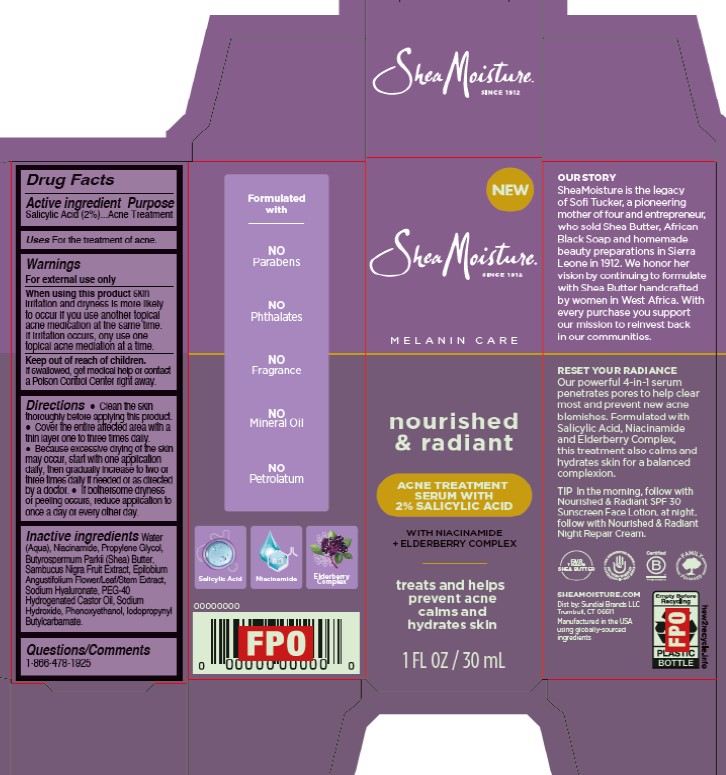 DRUG LABEL: Shea Moisture
NDC: 64942-2355 | Form: SOLUTION/ DROPS
Manufacturer: Conopco d/b/a/ Unilever
Category: otc | Type: HUMAN OTC DRUG LABEL
Date: 20250329

ACTIVE INGREDIENTS: SALICYLIC ACID 2 g/100 mL
INACTIVE INGREDIENTS: WATER; NIACINAMIDE; EUROPEAN ELDERBERRY; PEG-40 HYDROGENATED CASTOR OIL; IODOPROPYNYL BUTYLCARBAMATE; PROPYLENE GLYCOL; PHENOXYETHANOL; BUTYROSPERMUM PARKII (SHEA) BUTTER; EPILOBIUM ANGUSTIFOLIUM FLOWERING TOP; SODIUM HYALURONATE; SODIUM HYDROXIDE

Shea Moisture Nourished & Radiant Acne Treatment Serum With 2% Salicylic Acid

DESCRIPTION

Shea Moisture Nourished & Radiant Acne Treatment Serum With 2% Salicylic Acid

ACTIVE INGREDIENT

Salicylic Acid (2%)

PURPOSE

Acne Treatment

INDICATIONS AND USAGE

For the treatment of acne.

WARNINGS

For external use only. When using this product skin irritation and dryness is more likely to occur if you use another topical acne medication at the same time. If irritation occurs, only use one topical acne medication at a time. Keep out of reach of children.If swallowed, get medical help or contact a Poison Control Center right away.

Keep out of reach of children.If swallowed, get medical help or contact a Poison Control Center right away.

DOSAGE AND ADMINISTRATION

Clean the skin thoroughly before applying this product.

Cover the entire affected area with a thin layer one to three times daily.

Because excessive drying of the skin may occur, start with one application daily, then gradually increase to two or three times daily if needed or as directed by a doctor.

If bothersome dryness or peeling occurs, reduce application to once a day or every other day.

INACTIVE INGREDIENT

Water (Aqua), Niacinamide, Propylene Glycol, Butyrospermum Parkii (Shea) Butter, Sambucus Nigra Fruit Extract, Epilobium Angustifolium Flower/Leaf/Stem Extract, Sodium Hyaluronate, Peg-40 Hydrogenated Castor Oil, Sodium Hydroxide, Phenoxyethanol, Iodopropynyl Butylcarbamate

QUESTIONS

1-866-478-1925